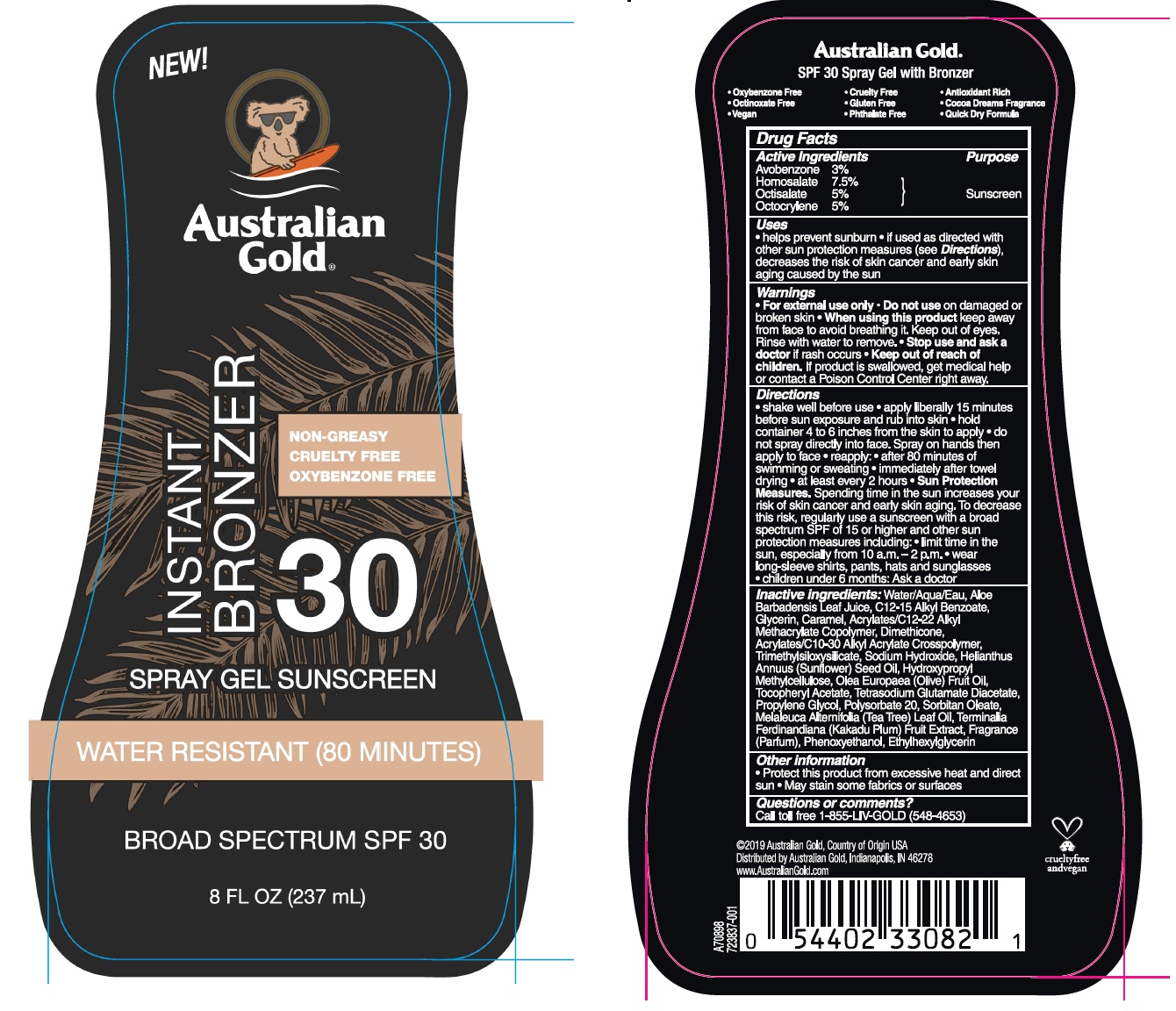 DRUG LABEL: Australian Gold
NDC: 58443-0275 | Form: SPRAY
Manufacturer: Prime Enterprises Inc.
Category: otc | Type: HUMAN OTC DRUG LABEL
Date: 20210112

ACTIVE INGREDIENTS: AVOBENZONE 29.4 mg/1 mL; HOMOSALATE 73.5 mg/1 mL; OCTISALATE 49 mg/1 mL; OCTOCRYLENE 49 mg/1 mL
INACTIVE INGREDIENTS: WATER; SUNFLOWER OIL; TEA TREE OIL; OLIVE OIL; PHENOXYETHANOL; POLYSORBATE 20; SORBITAN MONOOLEATE; ETHYLHEXYLGLYCERIN; KAKADU PLUM; TETRASODIUM GLUTAMATE DIACETATE; .ALPHA.-TOCOPHEROL ACETATE; TRIMETHYLSILOXYSILICATE (M/Q 1.0-1.2); CARBOMER INTERPOLYMER TYPE A (55000 CPS); BUTYL ACRYLATE/C16-C20 ALKYL METHACRYLATE/METHACRYLIC ACID/METHYL METHACRYLATE COPOLYMER; DIMETHICONE; HYPROMELLOSES; PROPYLENE GLYCOL; ALOE VERA LEAF; ALKYL (C12-15) BENZOATE; GLYCERIN; SODIUM HYDROXIDE; CARAMEL

Australian Gold Instant Bronzer 30 Spray Gel Sunscreen

Active Ingredients

Avobenzone 3%

Homosalate 7.5%

Octisalate 5%

Octocrylene 5%

Purpose

Sunscreen

Uses

- helps prevent sunburn • if used as directed with other sun protection measures (see Directions), decreases the risk of skin cancer and early skin aging caused by the sun

Warnings

- For external use only

- Do not use on damaged or broken skin

- When using this product keep away from face to avoid breathing it. Keep out of eyes.

Rinse with water to remove.

- Stop use and ask a doctor if rash occurs

- Keep out of reach of children. If product is swallowed, get medical help or contact a Poison Control Center right away.

Directions

- shake well before use • apply liberally 15 minutes before sun exposure and rub into skin • hold container 4 to 6 inches from the skin to apply • do not spray directly into face. Spray on hands then apply to face • reapply: • after 80 minutes of swimming or sweating • immediately after towel drying • at least every 2 hours • Sun Protection Measures. Spending time in the sun increases your risk of skin cancer and early skin aging. To decrease this risk regularly use a sunscreen with a broad spectrum SPF of 15 or higher and other sun protection measures including: • limit time in the sun, especially from 10 a.m. – 2 p.m. • wear long-sleeve shirts, pants, hats, and sunglasses • children under 6 months: Ask a doctor

Inactive ingredients

Water/Aqua/Eau, Aloe Barbadensis Leaf Juice, C12-15 Alkyl Benzoate, Glycerin, Caramel, Acrylates/C12-22 Alkyl Methacrylate Copolymer, Dimethicone, Acrylates/C10-30 Alkyl Acrylate Crosspolymer, Trimethylsiloxysilicate, Sodium Hydroxide, Helianthus Annuus (Sunflower) Seed Oil, Hydroxypropyl Methylcellulose, Olea Europaea (Olive) Fruit Oil, Tocopheryl Acetate, Tetrasodium Glutamate Diacetate, Propylene Glycol, Polysorbate 20, Sorbitan Oleate, Melaleuca Alternifolia (Tea Tree) Leaf Oil, Terminalia Ferdinandiana (Kakadu Plum) Fruit Extract, Fragrance (Parfum), Phenoxyethanol, Ethylhexylglycerin

Other information

- Protect this product from excessive heat and direct sun • May stain some fabrics or surfaces

Questions or comments?

Call toll free 1-855-LIV-GOLD (548-4653)